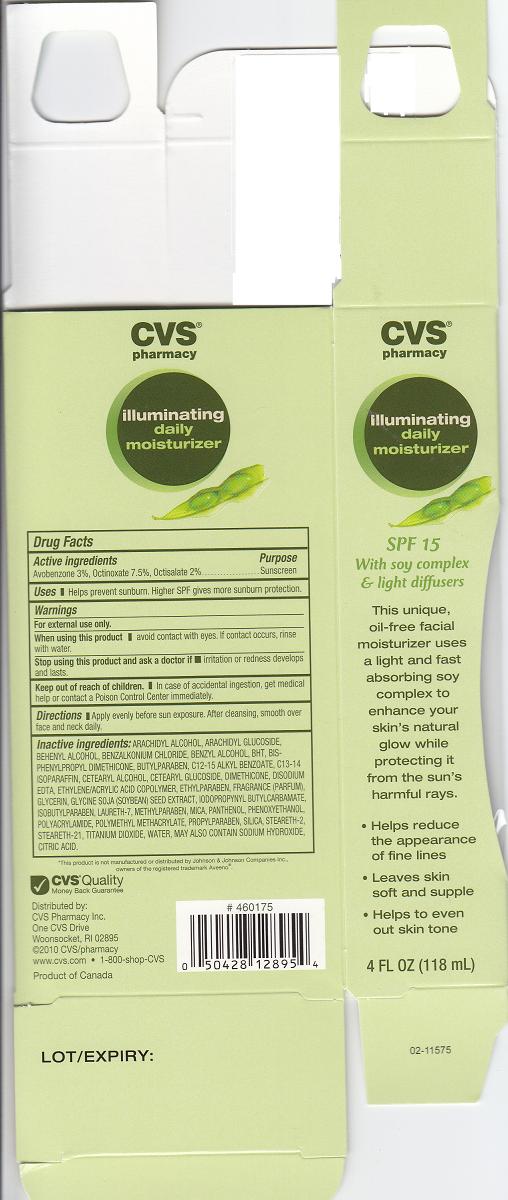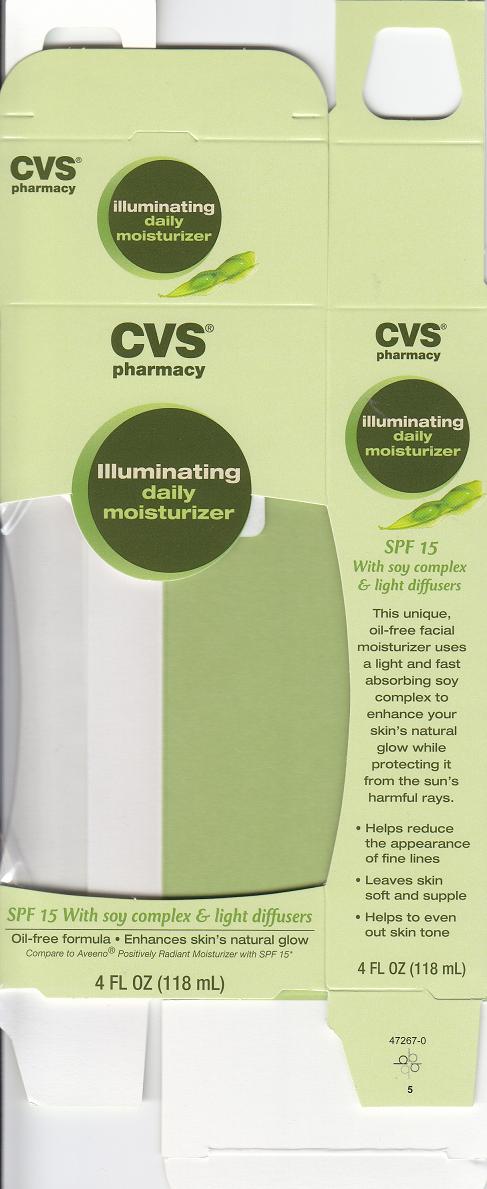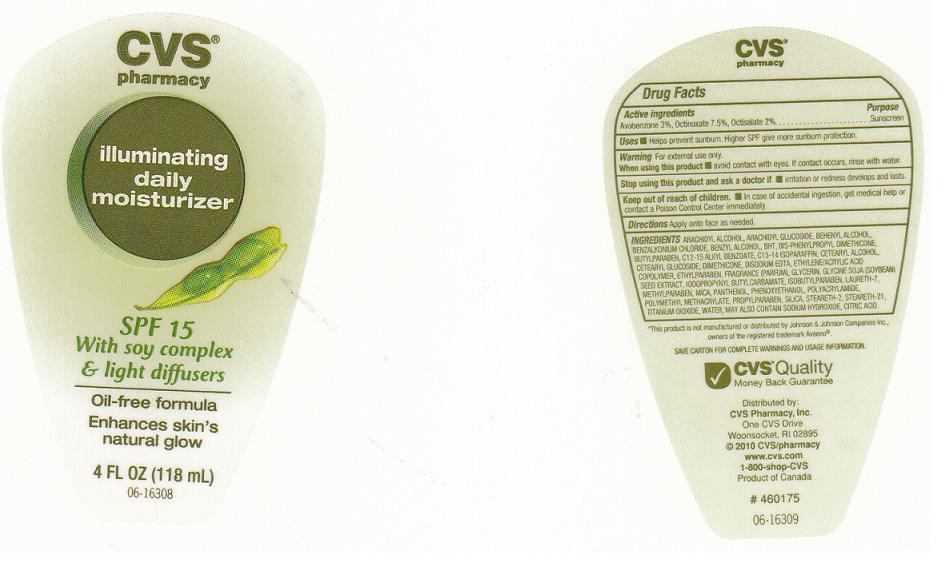 DRUG LABEL: ILLUMINATING DAILY MOISTURIZER
NDC: 59779-601 | Form: LOTION
Manufacturer: CVS PHARMACY INC
Category: otc | Type: HUMAN OTC DRUG LABEL
Date: 20100804

ACTIVE INGREDIENTS: AVOBENZONE 3.0000 mL/100 mL; OCTINOXATE 7.5000 mL/100 mL; OCTISALATE 2.0000 mL/100 mL

DRUG FACTS BOX

ACTIVE INGREDIENTS

- AVOBENZONE 3% (SUNSCREEN)
- OCTINOXATE 7.5% (SUNSCREEN)
- OCTISALATE 2% (SUNSCREEN)

USES AND DIRECTIONS

- USES: HELPS PREVENT SUNBURN. HIGHER SPF GIVES MORE SUNBURN PROTECTION.
- DIRECTIONS: APPLY EVENLY BEFORE SUN EXPOSURE. AFTER CLEANSING, SMOOTH OVER FACE AND NECK DAILY.

WARNINGS

- FOR EXTERNAL USE ONLY.

WHEN USING THIS PRODUCT

AVOID CONTACT WITH EYES. IF CONTACT OCCURS, RINSE WITH WATER.

STOP USE AND ASK A DOCTOR IF

RASH OR REDNESS DEVELOPS AND LASTS.

KEEP OUT OF REACH OF CHILDREN

IN CASE OF ACCIDENTAL INGESTION, GET MEDICAL HELP OR CONTACT A POISON CONTROL CENTER IMMEDIATELY.

OTHER INFORMATION

STORE AT ROOM TEMPERATURE.

PACKAGE LABELS/ CARTON

- Front and Back Labels: cvs4.jpg
- Carton: cvs1.jpg
- Carton: cvs2.jpg